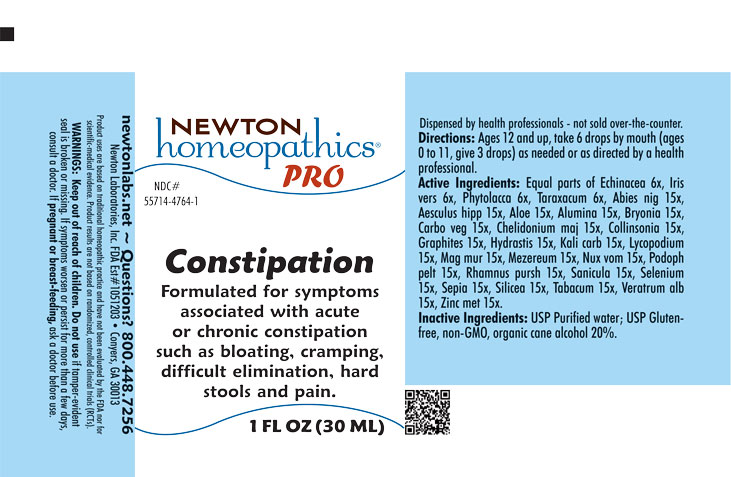 DRUG LABEL: Constipation
NDC: 55714-4764 | Form: LIQUID
Manufacturer: Newton Laboratories, Inc.
Category: homeopathic | Type: HUMAN OTC DRUG LABEL
Date: 20250725

ACTIVE INGREDIENTS: KRAMERIA LAPPACEA ROOT 15 [hp_X]/1 mL; PICEA MARIANA RESIN 15 [hp_X]/1 mL; HORSE CHESTNUT 15 [hp_X]/1 mL; ALOE 15 [hp_X]/1 mL; ALUMINUM OXIDE 15 [hp_X]/1 mL; BRYONIA ALBA ROOT 15 [hp_X]/1 mL; ACTIVATED CHARCOAL 15 [hp_X]/1 mL; CHELIDONIUM MAJUS 15 [hp_X]/1 mL; COLLINSONIA CANADENSIS ROOT 15 [hp_X]/1 mL; GRAPHITE 15 [hp_X]/1 mL; GOLDENSEAL 15 [hp_X]/1 mL; POTASSIUM CARBONATE 15 [hp_X]/1 mL; LYCOPODIUM CLAVATUM SPORE 15 [hp_X]/1 mL; MAGNESIUM CHLORIDE 15 [hp_X]/1 mL; DAPHNE MEZEREUM BARK 15 [hp_X]/1 mL; STRYCHNOS NUX-VOMICA SEED 15 [hp_X]/1 mL; PODOPHYLLUM 15 [hp_X]/1 mL; SANICULA EUROPAEA LEAF 15 [hp_X]/1 mL; SELENIUM 15 [hp_X]/1 mL; SEPIA OFFICINALIS JUICE 15 [hp_X]/1 mL; SILICON DIOXIDE 15 [hp_X]/1 mL; TOBACCO LEAF 15 [hp_X]/1 mL; VERATRUM ALBUM ROOT 15 [hp_X]/1 mL; ZINC 15 [hp_X]/1 mL; ECHINACEA, UNSPECIFIED 6 [hp_X]/1 mL; IRIS VERSICOLOR ROOT 6 [hp_X]/1 mL; PHYTOLACCA AMERICANA ROOT 6 [hp_X]/1 mL; TARAXACUM OFFICINALE 6 [hp_X]/1 mL
INACTIVE INGREDIENTS: ALCOHOL; WATER

Constipation 4764L

INDICATIONS & USAGE SECTION

Formulated for symptoms associated with acute or chronic constipation such as bloating, cramping, difficult elimination, hard stools and pain.

DOSAGE & ADMINISTRATION SECTION

Directions: Ages 12 and up, take 6 drops by mouth (ages 0 to 11, give 3 drops) as needed or as directed by a health professional.

OTC - ACTIVE INGREDIENT SECTION

Equal parts of Echinacea 6x, Iris vers. 6x, Phytolacca 6x, Taraxacum 6x, Abies nig. 15x, Aesculus hipp. 15x, Aloe 15x, Alumina 15x, Bryonia 15x, Carbo veg. 15x, Chelidonium majus 15x, Collinsonia 15x, Graphites 15x, Hydrastis 15x, Kali carb. 15x, Lycopodium 15x, Mag. mur. 15x, Mezereum 15x, Nux vom. 15x, Podoph. pelt. 15x, Rhamnus purshiana 15x, Sanicula 15x, Selenium 15x, Sepia 15x, Silicea 15x, Tabacum 15x, Veratrum alb. 15x, Zinc.met. 15x.

OTC - PURPOSE SECTION

Formulated for symptoms associated with acute or chronic constipation such as bloating, cramping, difficult elimination, hard stools and pain.

INACTIVE INGREDIENT SECTION

Inactive Ingredients: USP Purified Water; USP Gluten-free, non-GMO, organic cane alcohol 20%.

QUESTIONS SECTION

newtonlabs.net - Questions? 800.448.7256

Newton Laboratoires, Inc. Est # 1051203 - Conyers, GA 30013

WARNINGS SECTION

WARNINGS: Keep out of reach of children. Do not use if tamper-evident seal is broken or missing. If symptoms worsen or persist for more than a few days, consult a doctor. If pregnant or breast-feeding, as a doctor before use.

OTC - PREGNANCY OR BREAST FEEDING SECTION

If pregnant or breast-feeding, ask a doctor before use.

OTC - KEEP OUT OF REACH OF CHILDREN SECTION

Keep out of reach of children.